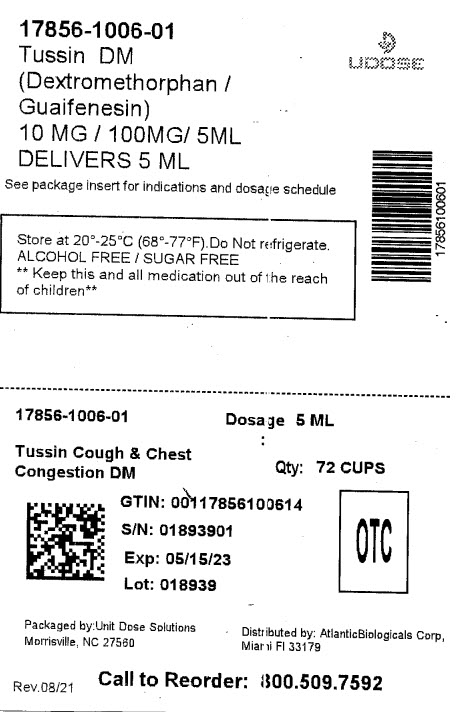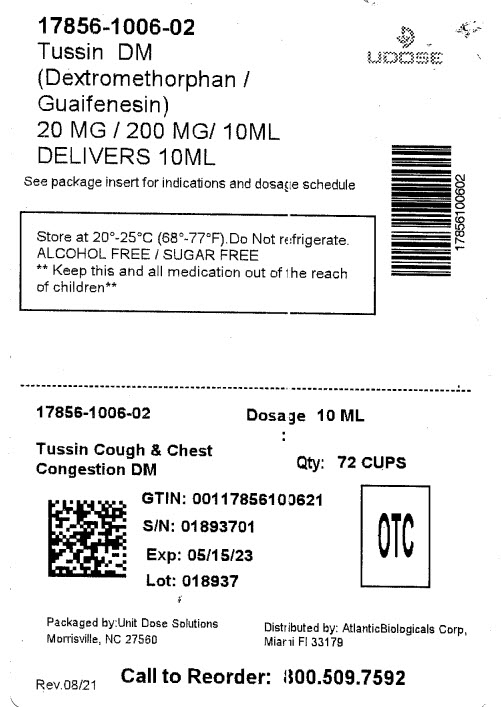 DRUG LABEL: Adult Tussin Cough and Chest Congestion DM Sugar Free
NDC: 17856-1006 | Form: LIQUID
Manufacturer: ATLANTIC BIOLOGICALS CORP.
Category: otc | Type: HUMAN OTC DRUG LABEL
Date: 20221111

ACTIVE INGREDIENTS: DEXTROMETHORPHAN HYDROBROMIDE 20 mg/10 mL; GUAIFENESIN 200 mg/10 mL
INACTIVE INGREDIENTS: ACESULFAME POTASSIUM; ANHYDROUS CITRIC ACID; GLYCERIN; MENTHOL; WATER; SORBITOL SOLUTION 70%; SODIUM CITRATE; SACCHARIN SODIUM; SODIUM BENZOATE

Drug Facts

Active ingredients (in each 10 mL)

Dextromethorphan HBr 20 mg

Guaifenesin 200 mg

Purposes

Cough suppressant

Expectorant

Uses

- temporarily relieves cough due to minor throat and bronchial irritation as may occur with a cold
- helps loosen phlegm (mucus) and thin bronchial secretions to drain bronchial tubes

Warnings

Do not use

if you are now taking a prescription monoamine oxidase inhibitor (MAOI) (certain drugs for depression, psychiatric or emotional conditions, or Parkinson’s disease), or for 2 weeks after stopping the MAOI drug. If you do not know if your prescription drug contains an MAOI, ask a doctor or pharmacist before taking this product.

Ask a doctor before use if you have

- cough that occurs with too much phlegm (mucus)
- cough that lasts or is chronic such as occurs with smoking, asthma, chronic bronchitis or emphysema

Stop use and ask a doctor if

cough lasts more than 7 days, comes back, or is accompanied by fever, rash, or persistent headache. These could be signs of a serious condition.

If pregnant or breast-feeding,

ask a health professional before use.

Keep out of reach of children.

In case of overdose, get medical help or contact a Poison Control Center right away (1-800-222-1222).

Directions

- do not take more than 6 doses in any 24-hour period
- measure only with dosing cup provided
- keep dosing cup with product
- mL= milliliter
- this adult product is not intended for use in children under 12 years of age
- adults and children 12 years and over: 10 mL every 4 hours
- children under 12 years: do not use

Other information

- Phenylketonurics: contains Phenylalanine 30 mg per 10 mL
- store between 20-25ºC(68-77ºF). Do not refrigerate

Inactive ingredients

acesulfame potassium, citric acid, flavor cherry, glycerin, menthol crystals, purified water, sorbitol solution 70%, sodium citrate, sodium saccharin, sodium benzoate.

Questions or comments?

DISTRIBUTED BY:

ATLANTIC BIOLOGICALS CORP

MIAMI, FL 33179